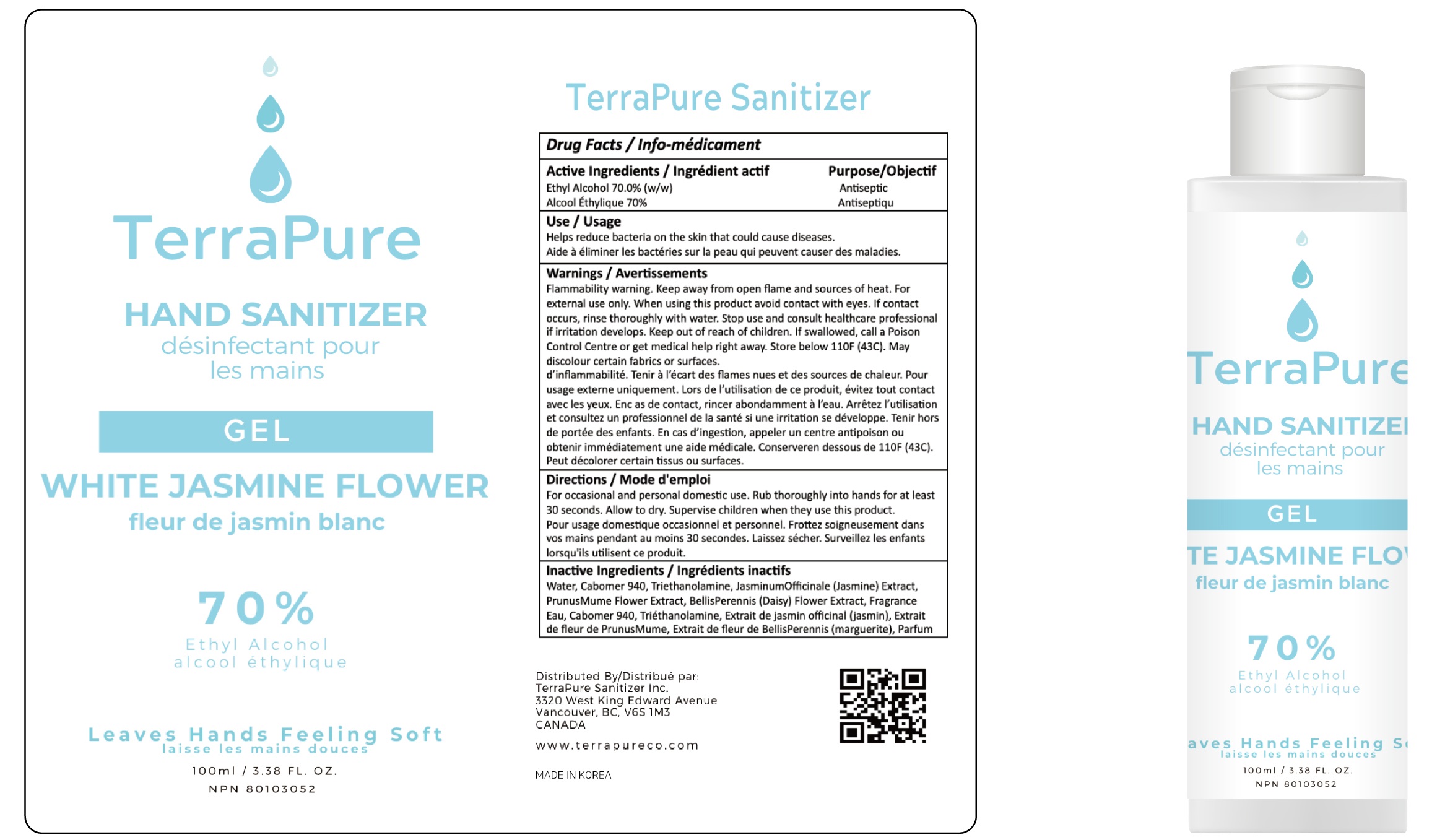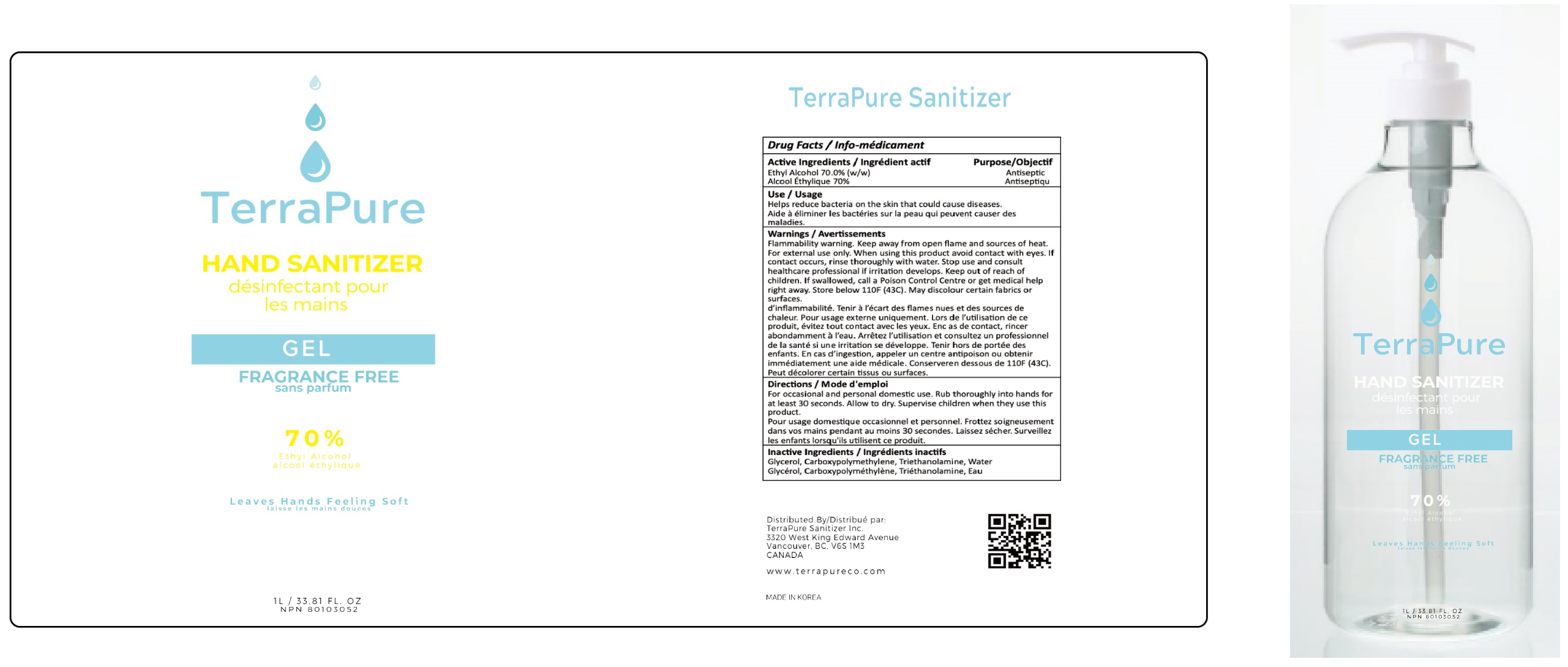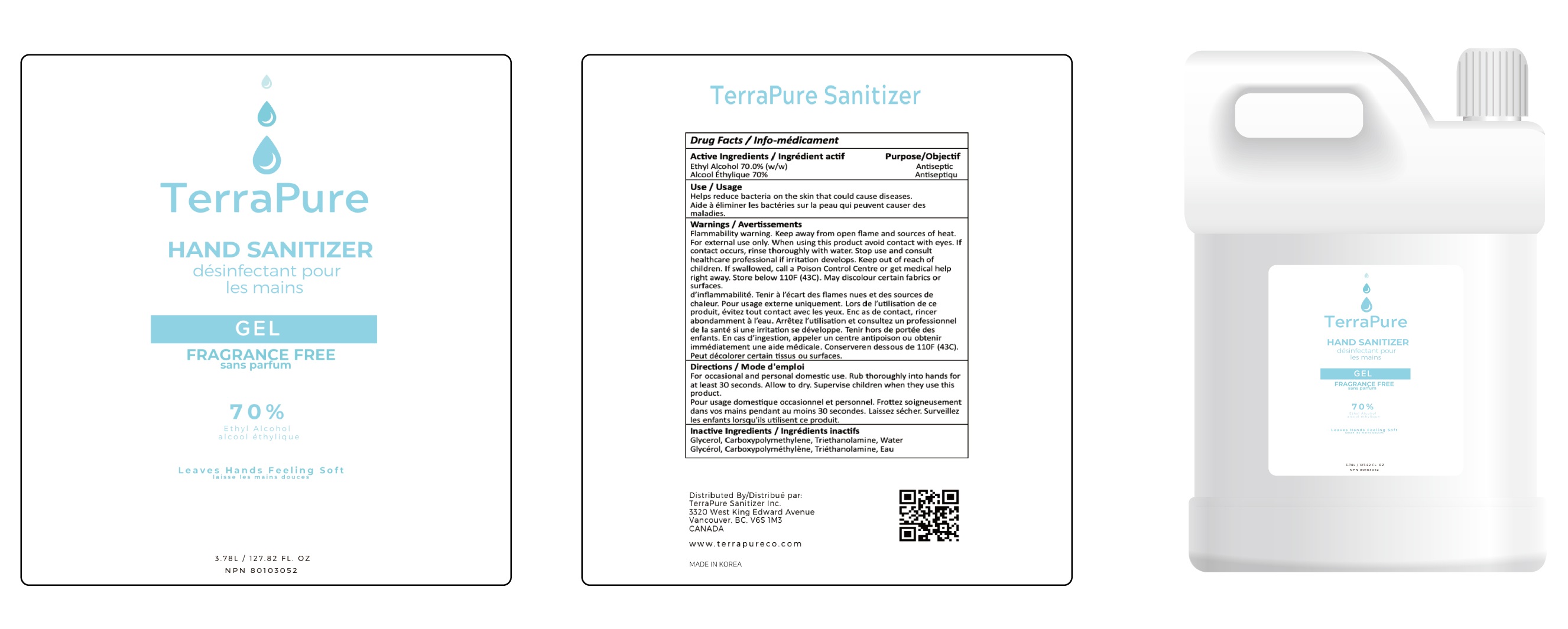 DRUG LABEL: TerraPure HAND SANITIZER
NDC: 75010-150 | Form: GEL
Manufacturer: Mirfeel Korea Co., Ltd
Category: otc | Type: HUMAN OTC DRUG LABEL
Date: 20201110

ACTIVE INGREDIENTS: Alcohol 70 mL/100 mL
INACTIVE INGREDIENTS: GLYCERIN

ACTIVE INGREDIENT

Active Ingredients / Ingrédient actif

Ethyl Alcohol 70.0% (w/w)

Alcool Éthylique 70%

INACTIVE INGREDIENTS

Inactive Ingredients / Ingrédients inactifs

Glycerol, Polyacrylic Acid, Nitrilotrisethanol, Dihydrogen Peroxide

Glycérol, Acide Polyacrylique, Nitrilotrisethanol, Oxyde de Dihydrogène

PURPOSE

Purpose/Objectif

Antiseptic / Antiseptiqu

WARNINGS

Warnings / Avertissements

Flammable. Keep away from open flame and sources of heat. For external use only. When using this product avoid contact with eyes. If contact occurs, rinse thoroughly with water. Stop use and consult healthcare professional if irritation develops. Keep out of reach of children. If swallowed, call a Poison Control Centre or get medical help right away. Store below 110F (43C). May discolour certain fabrics or surfaces.

Inflammable. Tenir à l’écart des flames nues et des sources de chaleur. Pour usage externe uniquement. Lors de l’utilisation de ce produit, évitez tout contact avec les yeux. Enc as de contact, rincer abondamment à l’eau. Arrêtez l’utilisation et consultez un professionnel de la santé si une irritation se développe. Tenir hors de portée des enfants. En cas d’ingestion, appeler un centre antipoison ou obtenir immédiatement une aide médicale. Conserveren dessous de 110F (43C). Peut décolorer certain tissus ou surfaces.

KEEP OUT OF REACH OF CHILDREN

Uses

Use / Usage

Helps reduce bacteria on the skin that could cause diseases.
Aide à éliminer les bactéries sur la peau qui peuvent causer des maladies.

Directions

Directions / Mode d'emploi

Press pump twice and rub throughout into hands for at least 30 seconds. Allow to dry. Children under 6 years of age should be supervised when using this product.

Appuyez deux fois sur la pompe et frottez-vous soigneusement dans les mains pendant au moins 30 secondes. Laissez sécher. Les enfants de moins de 6 ans doivent êtres surveillés lorsqu'ils utilisent ce produit.